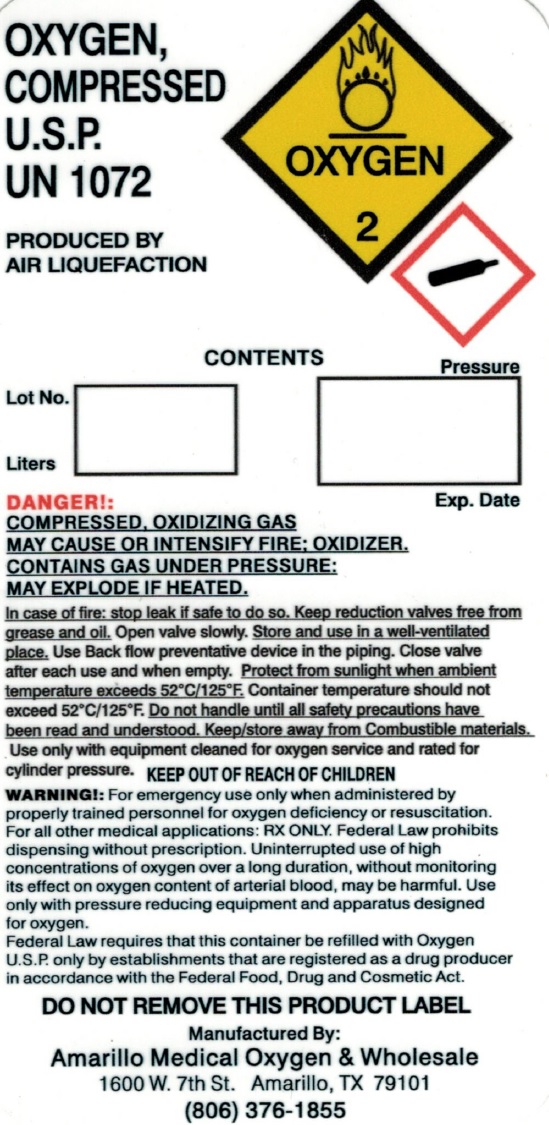 DRUG LABEL: Oxygen
NDC: 62137-002 | Form: GAS
Manufacturer: AMO Medical Oxygen, Inc.
Category: prescription | Type: HUMAN PRESCRIPTION DRUG LABEL
Date: 20201019

ACTIVE INGREDIENTS: OXYGEN 1 L/1 L

Oxygen-Gas